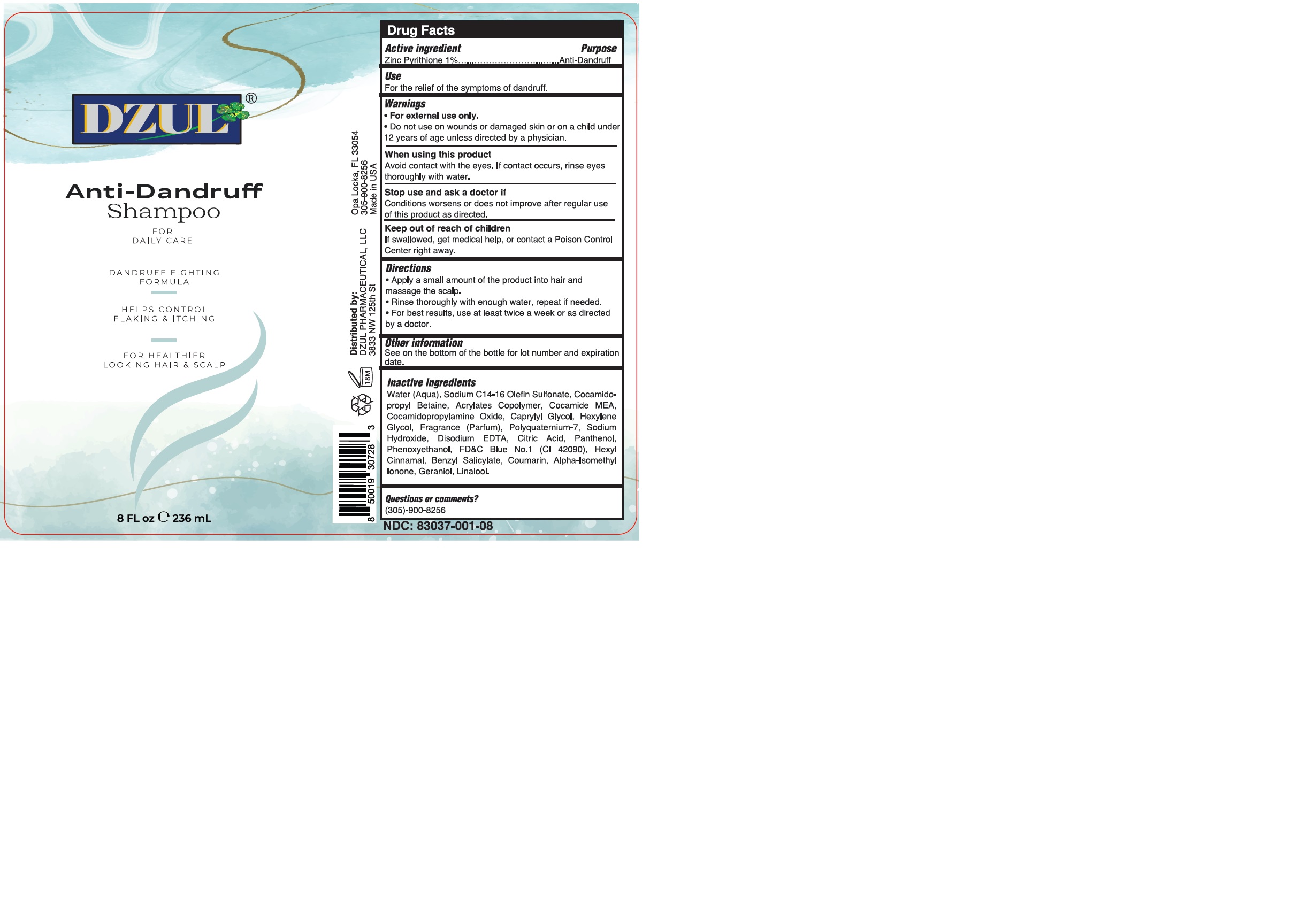 DRUG LABEL: DZUL ANTI-DANDRUFF
NDC: 83037-001 | Form: SHAMPOO
Manufacturer: Caball Sales, Inc.
Category: otc | Type: HUMAN OTC DRUG LABEL
Date: 20241122

ACTIVE INGREDIENTS: PYRITHIONE ZINC 1 g/100 mL
INACTIVE INGREDIENTS: COCO MONOETHANOLAMIDE; .ALPHA.-HEXYLCINNAMALDEHYDE; ANHYDROUS CITRIC ACID; SODIUM HYDROXIDE; WATER; SODIUM C14-16 OLEFIN SULFONATE; COCAMIDOPROPYLAMINE OXIDE; PHENOXYETHANOL; FD&C BLUE NO. 1; LINALOOL, (+)-; BENZYL SALICYLATE; COUMARIN; PANTHENOL; GERANIOL; COCAMIDOPROPYL BETAINE; CAPRYLYL GLYCOL; EDETATE DISODIUM; POLYQUATERNIUM-7 (70/30 ACRYLAMIDE/DADMAC; 1600 KD); ISOMETHYL-.ALPHA.-IONONE; HEXYLENE GLYCOL

83037-001-08

ACTIVE INGREDIENT

Zinc Pyrithione 1%

PURPOSE

Anti-Dandruff

INDICATIONS AND USAGE

For the relief of the symptoms of dandruff.

WARNINGS

For external use only.

Do not use on wounds or damaged skin or on a child under 12 years of age unless directed by a physician.

WHEN USING

Avoid contact with the eyes. If contact occurs, rinse eyes thoroughly with water.

STOP USE

Conditions worsens or does not improve after regular use of this product as directed.

KEEP OUT OF REACH OF CHILDREN

If swallowed, get medical help or contact Poison Control Center right away.

DOSAGE AND ADMINISTRATION

Apply a small amount quantity of the product into hair and massage the scalp.
Rinse thoroughly with enough water, repeat if needed.

For best results, use at least twice a week or as directed by a doctor.

OTHER SAFETY INFORMATION

See on the bottom of the bottle for lot number and expiration date.

INACTIVE INGREDIENT

Water (Aqua), Sodium C14-16 Olefin Sulfonate, Cocamidopropyl Betaine, Acrylates Copolymer, Cocamide MEA, Cocamidopropylamine Oxide, Caprylyl Glycol, Hexylene Glycol, Fragrance (Parfum), Polyquaternium-7, Sodium Hydroxide, Disodium EDTA, Citric Acid, Panthenol, Phenoxyethanol, FD&C Blue No.1 (CI 42090), Hexyl Cinnamal, Benzyl Salicylate, Coumarin, Alpha-Isomethyl Ionone, Geraniol, Linalool.

QUESTIONS

QUESTION OR COMMENTS?

Call (305)-900-8256